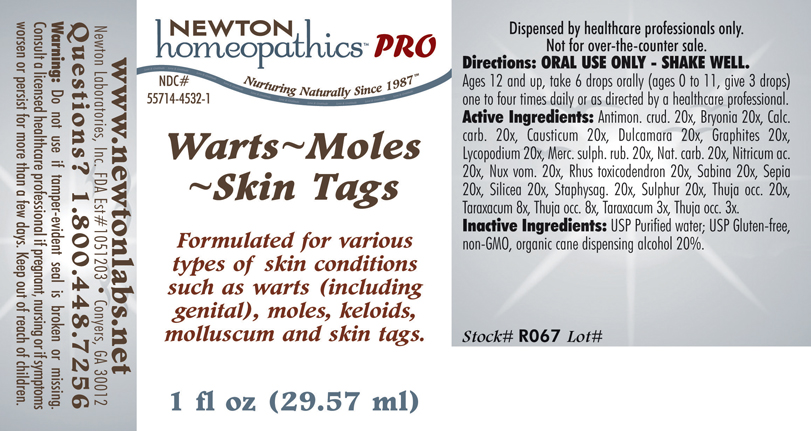 DRUG LABEL: Warts - Moles - Skin Tags 
NDC: 55714-4532 | Form: LIQUID
Manufacturer: Newton Laboratories, Inc.
Category: homeopathic | Type: HUMAN PRESCRIPTION DRUG LABEL
Date: 20110601

ACTIVE INGREDIENTS: Antimony Trisulfide 20 [hp_X]/1 mL; Bryonia Alba Root 20 [hp_X]/1 mL; Oyster Shell Calcium Carbonate, Crude 20 [hp_X]/1 mL; Causticum 20 [hp_X]/1 mL; Solanum Dulcamara Top 20 [hp_X]/1 mL; Graphite 20 [hp_X]/1 mL; Lycopodium Clavatum Spore 20 [hp_X]/1 mL; Mercuric Sulfide 20 [hp_X]/1 mL; Sodium Carbonate 20 [hp_X]/1 mL; Nitric Acid 20 [hp_X]/1 mL; Strychnos Nux-vomica Seed 20 [hp_X]/1 mL; Toxicodendron Pubescens Leaf 20 [hp_X]/1 mL; Juniperus Sabina Leafy Twig 20 [hp_X]/1 mL; Sepia Officinalis Juice 20 [hp_X]/1 mL; Silicon Dioxide 20 [hp_X]/1 mL; Delphinium Staphisagria Seed 20 [hp_X]/1 mL; Sulfur 20 [hp_X]/1 mL; Thuja Occidentalis Leafy Twig 20 [hp_X]/1 mL; Taraxacum Officinale 8 [hp_X]/1 mL
INACTIVE INGREDIENTS: Alcohol

Warts - Moles - Skin Tags

INDICATIONS & USAGE SECTION

Warts - Moles - Skin Tags Formulated for various types of skin conditions such as warts (including genital), moles, keloids, molluscum and skin tags.

DOSAGE & ADMINISTRATION SECTION

Directions: ORAL USE ONLY - SHAKE WELL. Ages 12 and up, take 6 drops orally (ages 0 to 11, give 3 drops) one to four times daily or as directed by a healthcare professional.

ACTIVE INGREDIENT SECTION

Antimon. crud. 20x, Bryonia 20x, Calc.carb. 20x, Causticum 20x, Dulcamara 20x, Graphites 20x, Lycopodium 20x, Merc. sulph. rub. 20x, Nat. carb. 20x, Nitricum ac. 20x, Nux vom. 20x, Rhus toxicodendron 20x, Sabina 20x, Sepia 20x, Silicea 20x, Staphysag. 20x, Sulphur 20x, Thuja occ. 20x, Taraxacum 8x, Thuja occ. 8x, Taraxacum 3x, Thuja occ. 3x.

PURPOSE SECTION

Formulated for various types of skin conditions such as warts (including genital), moles, keloids, molluscum and skin tags.

INACTIVE INGREDIENT SECTION

Inactive Ingredients: USP Purified Water; USP Gluten-free, non-GMO, organic cane dispensing alcohol 20%.

QUESTIONS? SECTION

www.newtonlabs.net Newton Laboratories, Inc. FDA Est # 1051203 - Conyers, GA 30012
Questions? 1.800.448.7256

WARNINGS SECTION

Warning: Do not use if tamper - evident seal is broken or missing. Consult a licensed healthcare professional if pregnant, nursing or if symptoms worsen or persist for more than a few days. Keep out of reach of children.

PREGNANCY OR BREAST FEEDING SECTION

Consult a licensed healthcare professional if pregnant, nursing or if symptoms worsen or persist for more than a few days

KEEP OUT OF REACH OF CHILDREN SECTION

Keep out of reach of children